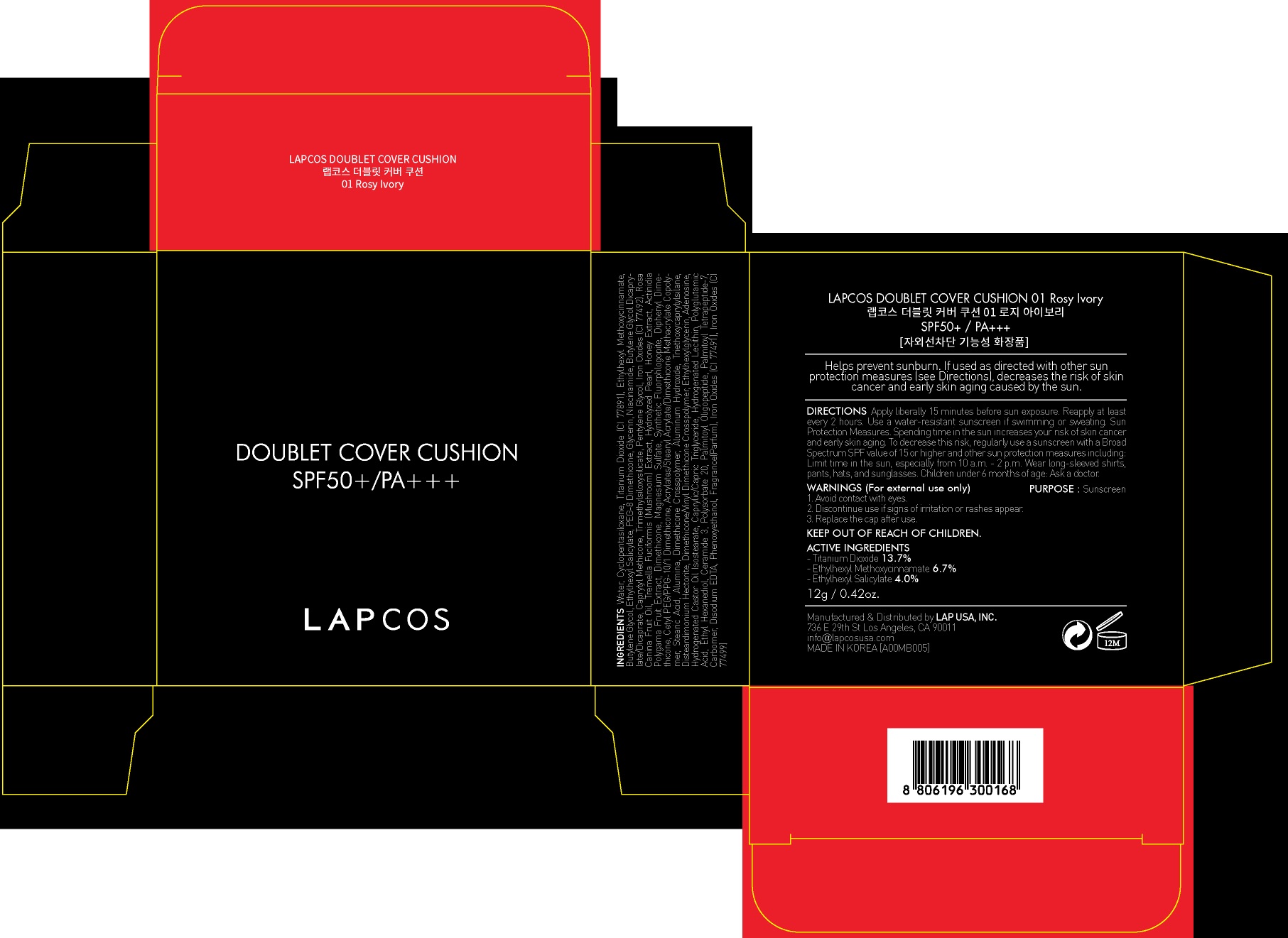 DRUG LABEL: LAPCOS Doublet Cover Cushion 01 Rosy Ivory
NDC: 71379-030 | Form: POWDER
Manufacturer: LAP CO.,LTD
Category: otc | Type: HUMAN OTC DRUG LABEL
Date: 20170504

ACTIVE INGREDIENTS: Titanium Dioxide 1.64 g/12 g; Octinoxate 0.80 g/12 g; Octisalate 0.48 g/12 g
INACTIVE INGREDIENTS: Water; Butylene Glycol

ACTIVE INGREDIENT

Active ingredients: Titanium Dioxide 13.7%, Ethylhexyl Methoxycinnamate 6.7%, Ethylhexyl Salicylate 4.0%

INACTIVE INGREDIENT

Inactive ingredients: Water, Cyclopentasiloxane, Butylene Glycol, PEG-8 Dimethicone, Glycerin, Niacinamide, Butylene Glycol Dicaprylate/Dicaprate, Caprylyl Methicone, Trimethylsiloxysilicate, Pentylene Glycol, Iron Oxides (CI 77492), Rosa Canina Fruit Oil, Tremella Fuciformis (Mushroom) Extract, Hydrolyzed Pearl, Honey Extract, Actinidia Polygama Fruit Extract, Dimethicone, Magnesium Sulfate, Synthetic Fluorphlogopite, Diphenyl Dimethicone, Cetyl PEG/PPG-10/1 Dimethicone, Acrylates/Stearyl Acrylate/Dimethicone Methacrylate Copolymer, Stearic Acid, Alumina, Dimethicone Crosspolymer, Aluminum Hydroxide, Triethoxycaprylylsilane, Disteardimonium Hectorite, Dimethicone/Vinyl Dimethicone Crosspolymer, Ethylhexylglycerin, Adenosine, Hydrogenated Castor Oil Isostearate, Caprylic/Capric Triglyceride, Hydrogenated Lecithin, Polyglutamic Acid, Ethyl Hexanediol, Ceramide 3, Polysorbate 20, Palmitoyl Oligopeptide, Palmitoyl Tetrapeptide-7, Carbomer, Disodium EDTA, Phenoxyethanol, Fragrance(Parfum), Iron Oxides (CI 77491), Iron Oxides (CI 77499)

PURPOSE

Purpose: Sunscreen

WARNINGS

Warnings: For external use only Avoid contact with eyes. Discontinue use if signs of irritation or rashes appear. Replace the cap after use. Keep Out of Reach of Children

DESCRIPTION

Uses: Helps prevent sunburn. If used as directed with other sun protection measures (see Directions), decreases the risk of skin cancer and early skin aging caused by the sun.

Directions: Apply liberally 15 minutes before sun exposure. Reapply at least every 2 hours. Use a water-resistant sunscreen if swimming or sweating. Sun Protection Measures. Spending time in the sun increases your risk of skin cancer and early skin aging. To decrease this risk, regularly use a sunscreen with a Broad Spectrum SPF value of 15 or higher and other sun protection measures including: Limit time in the sun, especially from 10 a.m. - 2 p.m. Wear long-sleeved shirts, pants, hats, and sunglasses. Children under 6 months of age: Ask a doctor.